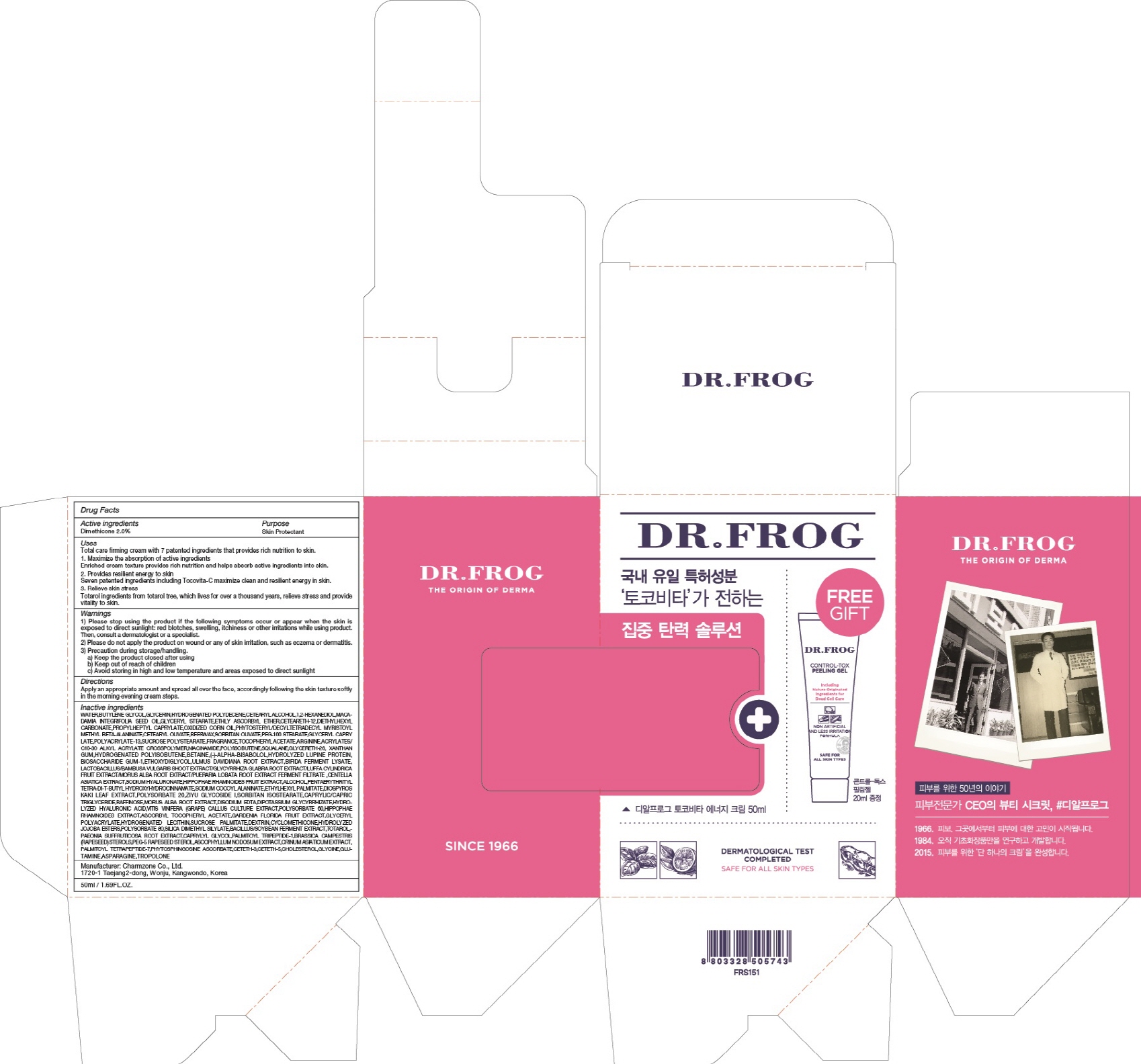 DRUG LABEL: DR FROG TOCOVITA ENERGY
NDC: 22201-1020 | Form: CREAM
Manufacturer: Charmzone Co Ltd
Category: otc | Type: HUMAN OTC DRUG LABEL
Date: 20180413

ACTIVE INGREDIENTS: Dimethicone 1.0 g/50 mL
INACTIVE INGREDIENTS: WATER; BUTYLENE GLYCOL

ACTIVE INGREDIENT

Active ingredients: Dimethicone 2.0%

INACTIVE INGREDIENT

Inactive ingredients:

WATER,BUTYLENE GLYCOL,GLYCERIN,HYDROGENATED POLYDECENE,CETEARYL ALCOHOL,1,2-HEXANEDIOL,MACADAMIA INTEGRIFOLIA SEED OIL,GLYCERYL STEARATE,ETHLY ASCORBYL ETHER,CETEARETH-12,DIETHYLHEXYL CARBONATE,PROPYLHEPTYL CAPRYLATE,OXIDIZED CORN OIL,PHYTOSTERYL/DECYLTETRADECYL MYRISTOYL METHYL BETA-ALANINATE,CETEARYL OLIVATE,BEESWAX,SORBITAN OLIVATE,PEG-100 STEARATE,GLYCERYL CAPRYLATE,POLYACRYLATE-13,SUCROSE POLYSTEARATE,FRAGRANCE,TOCOPHERYL ACETATE,ARGININE,ACRYLATES/C10-30 ALKYL ACRYLATE CROSSPOLYMER,NIACINAMIDE,POLYISOBUTENE,SQUALANE,GLYCERETH-26,XANTHAN GUM,HYDROGENATED POLYISOBUTENE,BETAINE,(-)-ALPHA-BISABOLOL,HYDROLYZED LUPINE PROTEIN,BIOSACCHARIDE GUM-1,ETHOXYDIGLYCOL,ULMUS DAVIDIANA ROOT EXTRACT,BIFIDA FERMENT LYSATE,LACTOBACILLUS/BAMBUSA VULGARIS SHOOT EXTRACT/GLYCYRRHIZA GLABRA ROOT EXTRACT/LUFFA CYLINDRICA FRUIT EXTRACT/MORUS ALBA ROOT EXTRACT/PUERARIA LOBATA ROOT EXTRACT FERMENT FILTRATE ,CENTELLA ASIATICA EXTRACT,SODIUM HYALURONATE,HIPPOPHAE RHAMNOIDES FRUIT EXTRACT,ALCOHOL,PENTAERYTHRITYL TETRA-DI-T-BUTYL HYDROXYHYDROCINNAMATE,SODIUM COCOYL ALANINATE,ETHYLHEXYL PALMITATE,DIOSPYROS KAKI LEAF EXTRACT,POLYSORBATE 20,ZIYU GLYCOSIDE I,SORBITAN ISOSTEARATE,CAPRYLIC/CAPRIC TRIGLYCERIDE,RAFFINOSE,MORUS ALBA ROOT EXTRACT,DISODIUM EDTA,DIPOTASSIUM GLYCYRRHIZATE,HYDROLYZED HYALURONIC ACID,VITIS VINIFERA (GRAPE) CALLUS CULTURE EXTRACT,POLYSORBATE 60,HIPPOPHAE RHAMNOIDES EXTRACT,ASCORBYL TOCOPHERYL ACETATE,GARDENIA FLORIDA FRUIT EXTRACT,GLYCERYL POLYACRYLATE,HYDROGENATED LECITHIN,SUCROSE PALMITATE,DEXTRIN,CYCLOMETHICONE,HYDROLYZED JOJOBA ESTERS,POLYSORBATE 80,SILICA DIMETHYL SILYLATE,BACILLUS/SOYBEAN FERMENT EXTRACT,TOTAROL,PAEONIA SUFFRUTICOSA ROOT EXTRACT,CAPRYLYL GLYCOL,PALMITOYL TRIPEPTIDE-1,BRASSICA CAMPESTRIS (RAPESEED) STEROLS,PEG-5 RAPESEED STEROL,ASCOPHYLLUM NODOSUM EXTRACT,CRINUM ASIATICUM EXTRACT,PALMITOYL TETRAPEPTIDE-7,PHYTOSPHINGOSINE ASCORBATE,CETETH-3,CETETH-5,CHOLESTEROL,GLYCINE,GLUTAMINE,ASPARAGINE,TROPOLONE

PURPOSE

Purpose: Skin Protectant

WARNINGS

1) Please stop using the product if the following symptoms occur or appear when the skin is exposed to direct sunlight: red blotches, swelling, itchiness or other irritations while using product. Then, consult a dermatologist or a specialist.

2) Please do not apply the product on wound or any of skin irritation, such as eczema or dermatitis.

3) Precaution during storage/handling. a) Keep the product closed after using b) Keep out of reach of children c) Avoid storing in high and low temperature and areas exposed to direct sunlight

KEEP OUT OF REACH OF CHILDREN

Uses

[Anti-wrinkle, Brightening]

Total care firming cream with 7 patented ingredients that provides rich nutrition to skin.

1. Maximize the absorption of active ingredients Enriched cream texture provides rich nutrition and helps absorb active ingredients into skin.

2. Provides resilient energy to skin Seven patented ingredients including Tocovita-C maximize clean and resilient energy in skin. 3. Relieve skin stress Totarol ingredients from totarol tree, which lives for over a thousand years, relieve stress and provide vitality to skin

Directions

Apply an appropriate amount and spread all over the face, accordingly following the skin texture softly in the morning∙evening cream steps.